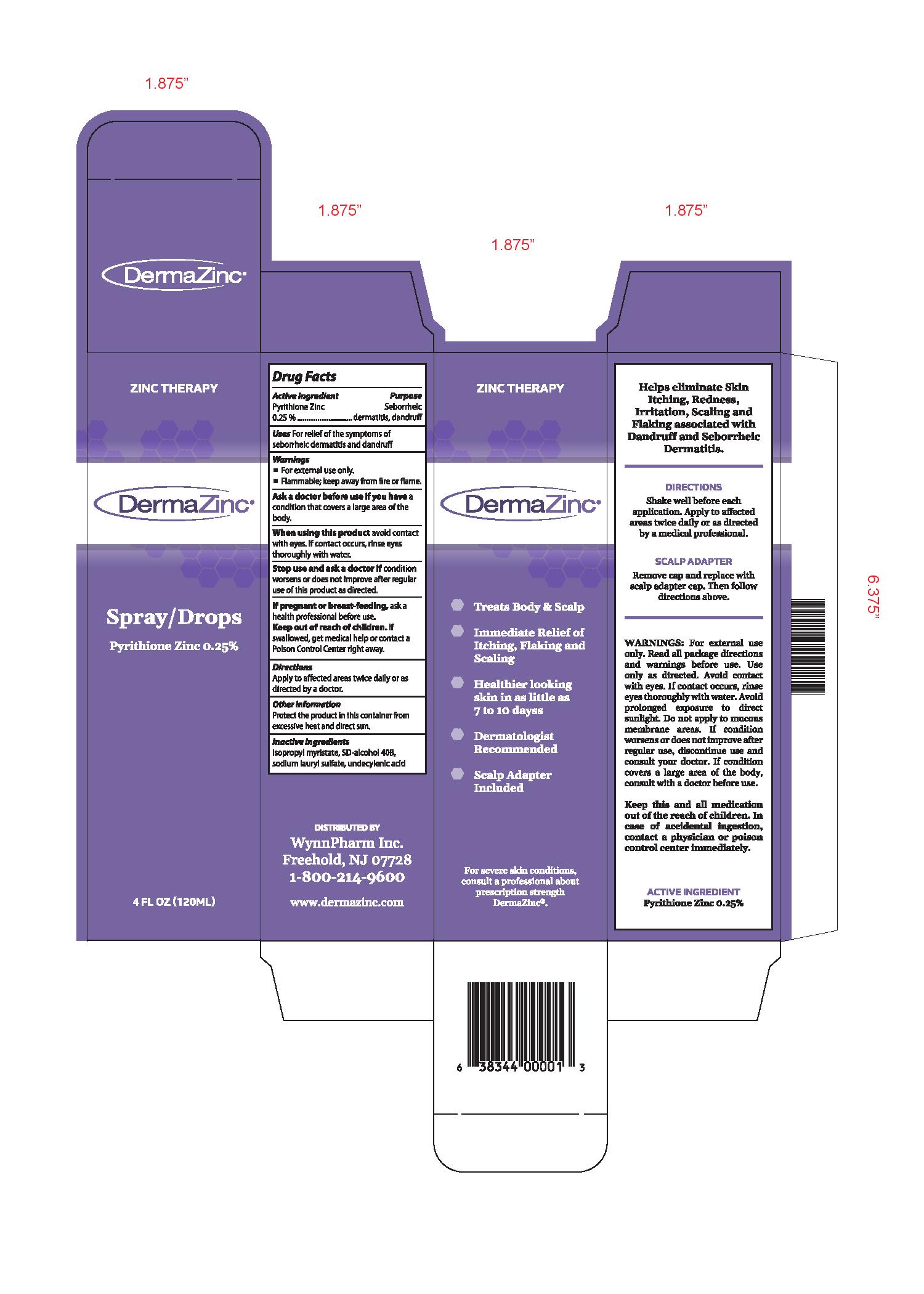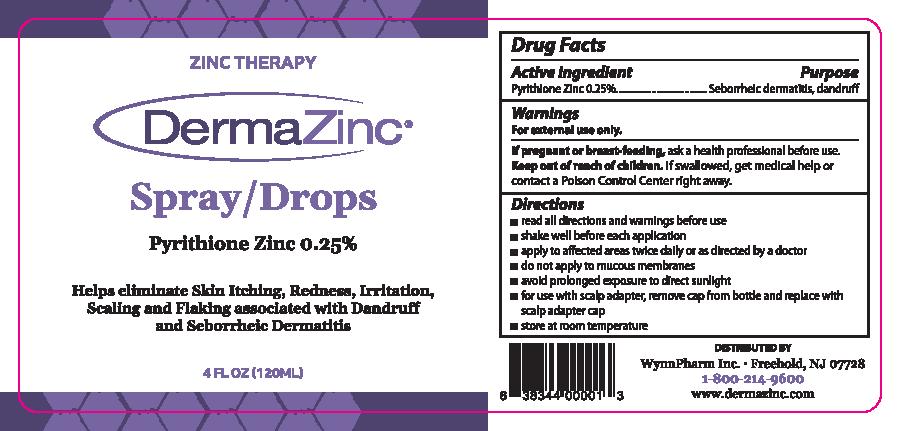 DRUG LABEL: DermaZinc
NDC: 35324-002 | Form: SPRAY
Manufacturer: WynnPharm Inc
Category: otc | Type: HUMAN OTC DRUG LABEL
Date: 20251114

ACTIVE INGREDIENTS: PYRITHIONE ZINC 0.25 g/100 mL
INACTIVE INGREDIENTS: ISOPROPYL MYRISTATE; UNDECYLENIC ACID; SODIUM LAURYL SULFATE; ALCOHOL

DermaZinc Spray/Drop

ACTIVE INGREDIENT

Pyrithione Zinc 0.25%

Keep Out of Reach of Children.

PURPOSE

Anti-dandruff

Seborrheic Dermatitis treatment

DOSAGE AND ADMINISTRATION

Apply to affected areas twice daily or as directed by a doctor.

INDICATIONS AND USAGE

For relief of the symptoms of seborrheic dermatitis and dandruff.

Warnings
■ For external use only.
■ Ask a doctor before use if you have a condition that covers a large area of the body.

When using this product avoid contact with the eyes. If contact occurs, rinse eyes thoroughly with
water.
Stop use and ask a doctor if condition worsens or does not improve after regular use of this
product as directed.

If pregnant or breast-feeding, ask a health professional before use. Keep out of reach of children.
If swallowed, get medical help or contact a Poison Control Center right away.

INACTIVE INGREDIENT

Isopropyl Myristate, SD-Alcohol 40-B, Sodium Lauryl Sulfate, Undecylinic Acid